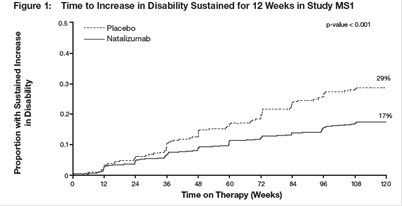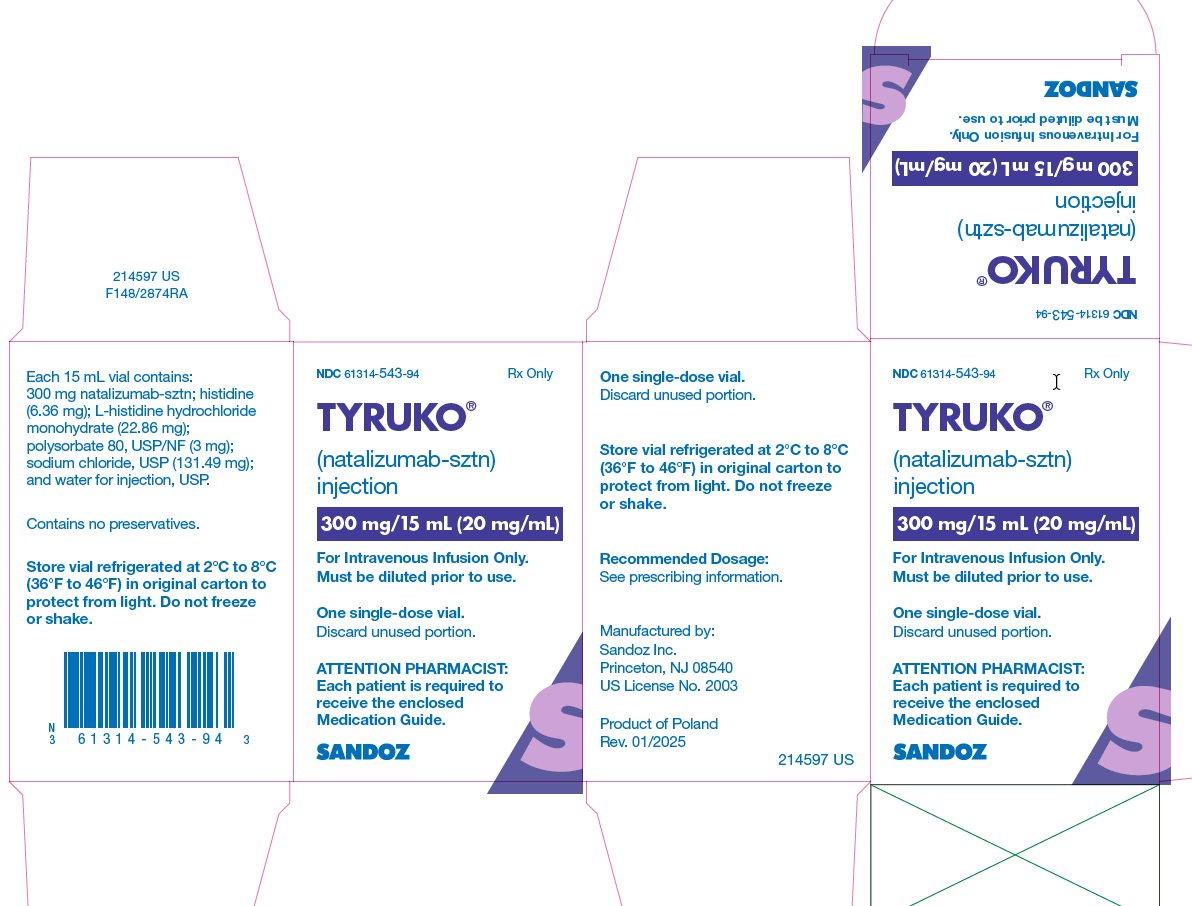 DRUG LABEL: TYRUKO
NDC: 61314-543 | Form: INJECTION
Manufacturer: Sandoz Inc
Category: prescription | Type: HUMAN PRESCRIPTION DRUG LABEL
Date: 20251031

ACTIVE INGREDIENTS: NATALIZUMAB 300 mg/15 mL
INACTIVE INGREDIENTS: SODIUM CHLORIDE 131.49 mg/15 mL; HISTIDINE MONOHYDROCHLORIDE MONOHYDRATE 22.86 mg/15 mL; HISTIDINE 6.36 mg/15 mL; POLYSORBATE 80 3 mg/15 mL; WATER

HIGHLIGHTS OF PRESCRIBING INFORMATION

These highlights do not include all the information needed to use TYRUKO® safely and effectively. See full prescribing information for TYRUKO.
TYRUKO (natalizumab-sztn) injection, for intravenous use
Initial U.S. Approval: 2023
TYRUKO (natalizumab-sztn) is biosimilar* to TYSABRI® (natalizumab).

RECENT MAJOR CHANGES

Warnings and Precautions (5.8) 10/2025

WARNING: PROGRESSIVE MULTIFOCAL LEUKOENCEPHALOPATHY

See full prescribing information for complete boxed warning

- Natalizumab products increase the risk of progressive multifocal leukoencephalopathy (PML), an opportunistic viral infection of the brain that usually leads to death or severe disability (5.1).
- Risk factors for the development of PML include the presence of anti-JCV antibodies, duration of therapy, and prior use of immunosuppressants. These factors should be considered in the context of expected benefit when initiating and continuing treatment with TYRUKO (5.1).
- Monitor patients, and withhold TYRUKO immediately at the first sign or symptom suggestive of PML (4, 5.1).
- Because of the risk of PML, TYRUKO is available only through a restricted distribution program called the TYRUKO REMS Program (5.1, 5.2).

1 INDICATIONS AND USAGE

TYRUKO is an integrin receptor antagonist indicated for treatment of:

Multiple Sclerosis (MS)

TYRUKO is indicated as monotherapy for the treatment of relapsing forms of multiple sclerosis, to include clinically isolated syndrome, relapsing-remitting disease, and active secondary progressive disease, in adults. Natalizumab products increase the risk of PML [see Warnings and Precautions (5.1)]. When initiating and continuing treatment with TYRUKO, physicians should consider whether the expected benefit of TYRUKO is sufficient to offset this risk. (1.1)

Crohn's Disease (CD)

- TYRUKO is indicated for inducing and maintaining clinical response and remission in adult patients with moderately to severely active Crohn's disease with evidence of inflammation who have had an inadequate response to, or are unable to tolerate, conventional CD therapies and inhibitors of TNF-α. (1.2)

Important Limitations:

- In CD, TYRUKO should not be used in combination with immunosuppressants or inhibitors of TNF-α. (1.2)

2 DOSAGE AND ADMINISTRATION

- 300 mg infused intravenously over one hour, every four weeks. Do not give as an intravenous push or bolus. (2.1, 2.2)
- TYRUKO solution must be administered within 4 hours of preparation. (2.3)
- Observe patients during all infusions. Post-infusion, for the first 12 infusions, observe patients for one hour after the infusion is complete. For patients who have received 12 infusions without evidence of a hypersensitivity reaction, observe patients post-infusion for the 13th and subsequent infusions according to clinical judgment. (2.4)
- In CD, discontinue in patients that have not experienced therapeutic benefit by 12 weeks of induction therapy, and in patients that cannot discontinue chronic concomitant steroids within six months of starting therapy. (2.2)

3 DOSAGE FORMS AND STRENGTHS

Injection: 300 mg/15 mL (20 mg/mL) solution in a single-dose vial for dilution prior to infusion (3)

4 CONTRAINDICATIONS

- Patients who have or have had PML (4)
- Patients who have had a hypersensitivity reaction to natalizumab products (4, 5.3)

5 WARNINGS AND PRECAUTIONS

- Herpes infections: Life-threatening and fatal cases have occurred with herpes encephalitis and meningitis infections. Blindness has occurred in patients developing acute retinal necrosis. Discontinue TYRUKO if these infections occur and treat appropriately. (5.3)
- Hepatotoxicity: Significant liver injury, including liver failure requiring transplant, has occurred. Discontinue TYRUKO in patients with evidence of liver injury. (5.4)
- Hypersensitivity reactions: Serious hypersensitivity reactions (e.g., anaphylaxis) have occurred. Permanently discontinue TYRUKO if such a reaction occurs. (5.5)
- Immunosuppression/Infections: Natalizumab products may increase the risk for certain infections. Monitor patients for development of infections due to increased risk with use of TYRUKO. (5.6)
- Hematological abnormalities: Natalizumab products may cause thrombocytopenia. Monitor patients for bleeding abnormalities. Discontinue TYRUKO in patients with thrombocytopenia. Neonatal thrombocytopenia and anemia have also occurred. Obtain a complete blood count in neonates exposed to TYRUKO in utero. (5.8)

6 ADVERSE REACTIONS

Most common adverse reactions (incidence ≥ 10%):

- MS - headache, fatigue, arthralgia, urinary tract infection, lower respiratory tract infection, gastroenteritis, vaginitis, depression, pain in extremity, abdominal discomfort, diarrhea NOS, and rash (6.1)
- CD - headache, upper respiratory tract infections, nausea, and fatigue (6.1)

To report SUSPECTED ADVERSE REACTIONS, contact Sandoz Inc. at 1-800-525-8747 or FDA at 1-800-FDA-1088 or www.fda.gov/medwatch.

8 USE IN SPECIFIC POPULATIONS

Pregnancy: Can cause fetal harm. (5.8, 8.1)

*Biosimilar means that the biological product is approved based on data demonstrating that it is highly similar to an FDA-approved biological product, known as a reference product, and that there are no clinically meaningful differences between the biosimilar product and the reference product. Biosimilarity of TYRUKO has been demonstrated for the condition(s) of use (e.g., indication(s), dosing regimen(s)), strength(s), dosage form(s), and route(s) of administration described in its Full Prescribing Information.

FULL PRESCRIBING INFORMATION

WARNING: PROGRESSIVE MULTIFOCAL LEUKOENCEPHALOPATHY

Natalizumab products increase the risk of progressive multifocal leukoencephalopathy (PML), an opportunistic viral infection of the brain that usually leads to death or severe disability. Risk factors for the development of PML include the presence of anti-JCV antibodies, duration of therapy, and prior use of immunosuppressants. These factors should be considered in the context of expected benefit when initiating and continuing treatment with TYRUKO [see Warnings and Precautions (5.1)].

- Healthcare professionals should monitor patients on TYRUKO for any new sign or symptom that may be suggestive of PML. TYRUKO dosing should be withheld immediately at the first sign or symptom suggestive of PML. For diagnosis, an evaluation that includes a gadolinium-enhanced magnetic resonance imaging (MRI) scan of the brain and, when indicated, cerebrospinal fluid analysis for JC viral DNA are recommended [see Contraindications (4), Warnings and Precautions (5.1)].

- Because of the risk of PML, TYRUKO is available only through a restricted program under a Risk Evaluation and Mitigation Strategy (REMS) called the TYRUKO REMS Program [see Warnings and Precautions (5.2)].

1 INDICATIONS AND USAGE

1.1 Multiple Sclerosis (MS)

TYRUKO is indicated as monotherapy for the treatment of relapsing forms of multiple sclerosis, to include clinically isolated syndrome, relapsing-remitting disease, and active secondary progressive disease, in adults. Natalizumab products increase the risk of PML [see Warnings and Precautions (5.1)]. When initiating and continuing treatment with TYRUKO, physicians should consider whether the expected benefit of TYRUKO is sufficient to offset this risk.

1.2 Crohn's Disease (CD)

TYRUKO is indicated for inducing and maintaining clinical response and remission in adult patients with moderately to severely active Crohn’s disease with evidence of inflammation who have had an inadequate response to, or are unable to tolerate, conventional CD therapies and inhibitors of TNF-α. TYRUKO should not be used in combination with immunosuppressants (e.g., 6-mercaptopurine, azathioprine, cyclosporine, or methotrexate) or inhibitors of TNF-α [see Warnings and Precautions (5.1)].

2 DOSAGE AND ADMINISTRATION

2.1 Multiple Sclerosis (MS)

Only prescribers registered in the MS TYRUKO REMS Program may prescribe TYRUKO for multiple sclerosis [see Warnings and Precautions (5.2)]. The recommended dose of TYRUKO for multiple sclerosis is 300 mg intravenous infusion over one hour every four weeks.

2.2 Crohn's Disease (CD)

Only prescribers registered in the CD TYRUKO REMS Program may prescribe TYRUKO for Crohn’s disease [see Warnings and Precautions (5.2)].

The recommended dose of TYRUKO for Crohn’s disease is 300 mg intravenous infusion over one hour every four weeks. TYRUKO should not be used with concomitant immunosuppressants (e.g., 6-mercaptopurine, azathioprine, cyclosporine, or methotrexate) or concomitant inhibitors of TNF-α. Aminosalicylates may be continued during treatment with TYRUKO.

If the patient with Crohn’s disease has not experienced therapeutic benefit by 12 weeks of induction therapy, discontinue TYRUKO. For patients with Crohn’s disease who start TYRUKO while on chronic oral corticosteroids, commence steroid tapering as soon as a therapeutic benefit of TYRUKO has occurred; if the patient with Crohn’s disease cannot be tapered off of oral corticosteroids within six months of starting TYRUKO, discontinue TYRUKO. Other than the initial six-month taper, prescribers should consider discontinuing TYRUKO for patients who require additional steroid use that exceeds three months in a calendar year to control their Crohn’s disease.

2.3 Dilution Instructions

1. Use aseptic technique when preparing TYRUKO solution for intravenous infusion. Each vial is intended for single use only. Discard any unused portion.

2. TYRUKO is a colorless and clear to slightly opalescent solution. Inspect the TYRUKO vial for particulate material and discoloration prior to dilution and administration. If visible particulates are observed and/or the liquid in the vial is discolored, the vial must not be used.
3. To prepare the diluted solution, withdraw 15 mL of TYRUKO from the vial using a sterile needle and syringe. Inject TYRUKO into 100 mL of 0.9% Sodium Chloride Injection, USP. No other intravenous diluents may be used to prepare the TYRUKO diluted solution.
4. Gently invert the TYRUKO diluted solution to mix completely. Do not shake. Inspect the solution visually for particulate material prior to administration.
5. The final dosage diluted solution has a concentration of 2.6 mg/mL.
6. Following dilution, infuse TYRUKO solution immediately, or refrigerate the diluted solution at 2°C to 8°C, and use within 4 hours. If stored at 2°C to 8°C, allow the diluted solution to warm to room temperature prior to infusion. DO NOT FREEZE.

2.4 Administration Instructions

- Infuse TYRUKO 300 mg in 100 mL 0.9% Sodium Chloride Injection, USP, over approximately one hour (infusion rate approximately 5 mg per minute). Do not administer TYRUKO as an intravenous push or bolus injection. After the infusion is complete, flush with 0.9% Sodium Chloride Injection, USP.
- Observe patients during all infusions. Promptly discontinue the infusion upon the first observation of any signs or symptoms consistent with a hypersensitivity-type reaction [see Warnings and Precautions (5.5)].
- Post-infusion, for the first 12 infusions, observe patients for one hour after the infusion is complete. For patients who have received 12 infusions without evidence of a hypersensitivity reaction, observe patients post-infusion for the 13th and subsequent infusions according to clinical judgment.
- Use of filtration devices during administration has not been evaluated. Other medications should not be injected into infusion set side ports or mixed with TYRUKO.

3 DOSAGE FORMS AND STRENGTHS

Injection: 300 mg/15 mL (20 mg/mL) colorless and clear to slightly opalescent solution in a single-dose vial for dilution prior to infusion.

4 CONTRAINDICATIONS

- TYRUKO is contraindicated in patients who have or have had progressive multifocal leukoencephalopathy (PML) [see Warnings and Precautions (5.1)].
- TYRUKO is contraindicated in patients who have had a hypersensitivity reaction to natalizumab products or any of the ingredients in TYRUKO. Observed reactions range from urticaria to anaphylaxis [see Warnings and Precautions (5.5)].

5 WARNINGS AND PRECAUTIONS

5.1 Progressive Multifocal Leukoencephalopathy

Progressive multifocal leukoencephalopathy (PML), an opportunistic viral infection of the brain caused by the JC virus (JCV) that typically only occurs in patients who are immunocompromised, and that usually leads to death or severe disability, has occurred in patients who have received natalizumab products.

Three factors that are known to increase the risk of PML in natalizumab-treated patients have been identified:

- The presence of anti-JCV antibodies. Patients who are anti-JCV antibody positive have a higher risk for developing PML.
- Longer treatment duration, especially beyond 2 years.
- Prior treatment with an immunosuppressant (e.g., mitoxantrone, azathioprine, methotrexate, cyclophosphamide, mycophenolate mofetil).

These factors should be considered in the context of expected benefit when initiating and continuing treatment with TYRUKO.

Table 1: Estimated United States Incidence of PML Stratified by Risk Factor
Anti-JCV Antibody Negative | Natalizumab Exposure | Anti-JCV Antibody Positive
Anti-JCV Antibody Negative | Natalizumab Exposure | No Prior Immunosuppressant Use | Prior Immunosuppressant Use
1/10,000 | 1-24 months | <1/1,000 | 1/1,000
1/10,000 | 25-48 months | 2/1,000 | 6/1,000
1/10,000 | 49-72 months | 4/1,000 | 7/1,000
1/10,000 | 73-96 months | 2/1,000 | 6/1,000

Notes: The risk estimates are based on postmarketing data in the United States from approximately 100,000 natalizumab exposed patients.

The anti-JCV antibody status was determined using an anti-JCV antibody test (ELISA) that has been analytically and clinically validated and is configured with detection and inhibition steps to confirm the presence of JCV-specific antibodies with an analytical false negative rate of 3%.

Retrospective analyses of postmarketing data from various sources, including observational studies and spontaneous reports obtained worldwide, suggest that the risk of developing PML may be associated with relative levels of serum anti-JCV antibody compared to a calibrator as measured by ELISA (often described as an anti-JCV antibody index value).

Ordinarily, patients receiving chronic immunosuppressant or immunomodulatory therapy or who have systemic medical conditions resulting in significantly compromised immune system function should not be treated with TYRUKO. Infection by the JC virus is required for the development of PML. Anti-JCV antibody testing should not be used to diagnose PML. Anti-JCV antibody negative status indicates that antibodies to the JC virus have not been detected. Patients who are anti-JCV antibody negative have a lower risk of PML than those who are positive. Patients who are anti-JCV antibody negative are still at risk for the development of PML due to the potential for a new JCV infection or a false negative test result. The reported rate of seroconversion in patients with MS (changing from anti-JCV antibody negative to positive and remaining positive in subsequent testing) is 3 to 8 percent annually. In addition, some patients’ serostatus may change intermittently. Therefore, patients with a negative anti-JCV antibody test result should be retested periodically. For purposes of risk assessment, a patient with a positive anti-JCV antibody test at any time is considered anti-JCV antibody positive regardless of the results of any prior or subsequent anti-JCV antibody testing. When assessed, anti-JCV antibody status should be determined using an analytically and clinically validated immunoassay. After plasma exchange (PLEX), wait at least two weeks to test for anti-JCV antibodies to avoid false negative test results caused by the removal of serum antibodies. After infusion of intravenous immunoglobulin (IVIg), wait at least 6 months (5 half-lives) for the IVIg to clear in order to avoid false positive anti-JCV antibody test results.

Healthcare professionals should monitor patients on TYRUKO for any new sign or symptom suggestive of PML. Symptoms associated with PML are diverse, progress over days to weeks, and include progressive weakness on one side of the body or clumsiness of limbs, disturbance of vision, and changes in thinking, memory, and orientation leading to confusion and personality changes. The progression of deficits usually leads to death or severe disability over weeks or months. Withhold TYRUKO dosing immediately and perform an appropriate diagnostic evaluation at the first sign or symptom suggestive of PML.

MRI findings may be apparent before clinical signs or symptoms. Cases of PML, diagnosed based on MRI findings and the detection of JCV DNA in the cerebrospinal fluid in the absence of clinical signs or symptoms specific to PML, have been reported. Many of these patients subsequently became symptomatic with PML. Therefore, monitoring with MRI for signs that may be consistent with PML may be useful, and any suspicious findings should lead to further investigation to allow for an early diagnosis of PML, if present. Consider monitoring patients at high risk for PML more frequently.

Lower PML-related mortality and morbidity have been reported following natalizumab products discontinuation in patients with PML who were initially asymptomatic compared to patients with PML who had characteristic clinical signs and symptoms at diagnosis. It is not known whether these differences are due to early detection and discontinuation of natalizumab products or due to differences in disease in these patients.

There are no known interventions that can reliably prevent PML or that can adequately treat PML if it occurs. PML has been reported following discontinuation of natalizumab products in patients who did not have findings suggestive of PML at the time of discontinuation. Patients should continue to be monitored for any new signs or symptoms that may be suggestive of PML for at least six months following discontinuation of TYRUKO.

Because of the risk of PML, TYRUKO is available only under a restricted distribution program, the TYRUKO REMS Program.

In multiple sclerosis patients, an MRI scan should be obtained prior to initiating therapy with TYRUKO. This MRI may be helpful in differentiating subsequent multiple sclerosis symptoms from PML.

In Crohn’s disease patients, a baseline brain MRI may also be helpful to distinguish pre-existent lesions from newly developed lesions, but brain lesions at baseline that could cause diagnostic difficulty while on natalizumab product therapy are uncommon.

For diagnosis of PML, an evaluation including a gadolinium-enhanced MRI scan of the brain and, when indicated, cerebrospinal fluid analysis for JC viral DNA are recommended. If the initial evaluations for PML are negative but clinical suspicion for PML remains, continue to withhold TYRUKO dosing, and repeat the evaluations.

There are no known interventions that can adequately treat PML if it occurs. Three sessions of PLEX over 5 to 8 days were shown to accelerate natalizumab clearance in a study of 12 patients with MS who did not have PML, although in the majority of patients, alpha-4 integrin receptor binding remained high. Adverse events which may occur during PLEX include clearance of other medications and volume shifts, which have the potential to lead to hypotension or pulmonary edema. Although PLEX has not been prospectively studied in natalizumab-treated patients with PML, it has been used in such patients in the postmarketing setting to remove natalizumab more quickly from the circulation. There is no evidence that PLEX has any benefit in the treatment of opportunistic infections such as PML.

JC virus infection of granule cell neurons in the cerebellum (i.e., JC virus granule cell neuronopathy [JCV GCN]) has been reported in patients treated with natalizumab products. JCV GCN can occur with or without concomitant PML. JCV GCN can cause cerebellar dysfunction (e.g., ataxia, incoordination, apraxia, visual disorders), and neuroimaging can show cerebellar atrophy. For diagnosis of JCV GCN, an evaluation that includes a gadolinium-enhanced MRI scan of the brain and, when indicated, cerebrospinal fluid analysis for JC viral DNA, is recommended. JCV GCN should be managed similarly to PML.

Immune reconstitution inflammatory syndrome (IRIS) has been reported in the majority of natalizumab product-treated patients who developed PML and subsequently discontinued natalizumab products. In almost all cases, IRIS occurred after PLEX was used to eliminate circulating natalizumab products. It presents as a clinical decline in the patient’s condition after natalizumab product removal (and in some cases after apparent clinical improvement) that may be rapid, can lead to serious neurological complications or death, and is often associated with characteristic changes in the MRI. Natalizumab products have not been associated with IRIS in patients discontinuing treatment with natalizumab products for reasons unrelated to PML. In natalizumab product-treated patients with PML, IRIS has been reported within days to several weeks after PLEX. Monitoring for development of IRIS and appropriate treatment of the associated inflammation should be undertaken.

5.2 TYRUKO REMS Program

TYRUKO is available only through a restricted program under a REMS called the TYRUKO REMS Program because of the risk of PML [see Warnings and Precautions (5.1)].

For prescribers and patients, the TYRUKO REMS Program has two components: MS TYRUKO REMS (for patients with multiple sclerosis) and CD TYRUKO REMS (for patients with Crohn’s disease).

Selected requirements of the TYRUKO REMS Program include the following:

- Prescribers must be certified and comply with the following:
  - Review the TYRUKO REMS Program prescriber educational materials, including the full prescribing information.
  - Review, complete, and sign the Prescriber Enrollment Form.
  - Educate patients on the benefits and risks of treatment with TYRUKO, ensure that patients receive the Medication Guide, and encourage them to ask questions.
  - Review, complete, and sign the Patient Enrollment Form for each patient.
  - Evaluate patients three months after the first infusion, six months after the first infusion, every six months thereafter, and for at least six months after discontinuing TYRUKO.
  - Determine every six months whether patients should continue on treatment and, if so, authorize treatment for another six months.
  - Submit to Sandoz Inc. the “TYRUKO Patient Status Report and Reauthorization Questionnaire” six months after initiating treatment and every six months thereafter.
  - Complete an “Initial Discontinuation Questionnaire” when TYRUKO is discontinued, and a “6-Month Discontinuation Questionnaire” following discontinuation of TYRUKO.
  - Report cases of PML, hospitalizations due to opportunistic infections, and deaths to Sandoz Inc. at 1-800-525-8747 as soon as possible.
- Patients must be enrolled in the TYRUKO REMS Program, read the Medication Guide, understand the risks associated with TYRUKO, and complete and sign the Patient Enrollment Form.
- Pharmacies and infusion centers must be specially certified to dispense or infuse TYRUKO.

5.3 Herpes Infections

Herpes Encephalitis and Meningitis

Natalizumab products increase the risk of developing encephalitis and meningitis caused by herpes simplex and varicella zoster viruses. Serious, life-threatening, and sometimes fatal cases have been reported in the postmarketing setting in multiple sclerosis patients receiving natalizumab products. Laboratory confirmation in those cases was based on positive PCR for viral DNA in the cerebrospinal fluid. The duration of treatment with natalizumab products prior to onset ranged from a few months to several years. Monitor patients receiving TYRUKO for signs and symptoms of meningitis and encephalitis. If herpes encephalitis or meningitis occurs, TYRUKO should be discontinued, and appropriate treatment for herpes encephalitis/meningitis should be administered.

Acute Retinal Necrosis

Acute retinal necrosis (ARN) is a fulminant viral infection of the retina caused by the family of herpes viruses (e.g., varicella zoster, herpes simplex virus). A higher risk of ARN has been observed in patients being administered natalizumab products. Patients presenting with eye symptoms, including decreased visual acuity, redness, or eye pain, should be referred for retinal screening for ARN. Some ARN cases occurred in patients with central nervous system (CNS) herpes infections (e.g., herpes meningitis or encephalitis). Serious cases of ARN led to blindness of one or both eyes in some patients. Following clinical diagnosis of ARN, consider discontinuation of TYRUKO. The treatment reported in ARN cases included anti-viral therapy and, in some cases, surgery.

5.4 Hepatotoxicity

Clinically significant liver injury, including acute liver failure requiring transplant, has been reported in patients treated with natalizumab products in the postmarketing setting. Signs of liver injury, including markedly elevated serum hepatic enzymes and elevated total bilirubin, occurred as early as six days after the first dose; signs of liver injury have also been reported for the first time after multiple doses. In some patients, liver injury recurred upon rechallenge, providing evidence that natalizumab products caused the injury. The combination of transaminase elevations and elevated bilirubin without evidence of obstruction is generally recognized as an important predictor of severe liver injury that may lead to death or the need for a liver transplant in some patients.

TYRUKO should be discontinued in patients with jaundice or other evidence of significant liver injury (e.g., laboratory evidence).

5.5 Hypersensitivity/Antibody Formation

Hypersensitivity reactions have occurred in patients receiving natalizumab products, including serious systemic reactions (e.g., anaphylaxis), which occurred at an incidence of <1%. These reactions usually occur within two hours of the start of the infusion. Symptoms associated with these reactions can include urticaria, dizziness, fever, rash, rigors, pruritus, nausea, flushing, hypotension, dyspnea, and chest pain. Generally, these reactions are associated with antibodies to natalizumab products.

If a hypersensitivity reaction occurs, discontinue administration of TYRUKO, and initiate appropriate therapy. Patients who experience a hypersensitivity reaction should not be re-treated with TYRUKO. Hypersensitivity reactions were more frequent in patients with antibodies to natalizumab compared to patients who did not develop antibodies to natalizumab in both MS and CD studies. Therefore, the possibility of antibodies to TYRUKO should be considered in patients who have hypersensitivity reactions [see Adverse Reactions (6.2)].

Antibody testing: If the presence of persistent antibodies is suspected, antibody testing should be performed. Antibodies may be detected and confirmed with sequential serum antibody tests.

Antibodies detected early in the treatment course (e.g., within the first six months) may be transient and may disappear with continued dosing. It is recommended that testing be repeated three months after an initial positive result to confirm that antibodies are persistent. Prescribers should consider the overall benefits and risks of TYRUKO in a patient with persistent antibodies.

Patients who receive natalizumab products for a short exposure (1 to 2 infusions) followed by an extended period without treatment are at higher risk of developing anti-drug antibodies and/or hypersensitivity reactions on re-exposure, compared to patients who received regularly scheduled treatment. Given that patients with persistent antibodies to natalizumab products experience reduced efficacy, and that hypersensitivity reactions are more common in such patients, consideration should be given to testing for the presence of antibodies in patients who wish to recommence therapy following a dose interruption. Following a period of dose interruption, patients testing negative for antibodies prior to re-dosing have a risk of antibody development with re-treatment that is similar to natalizumab product naïve patients [see Adverse Reactions (6.2)].

5.6 Immunosuppression/Infections

The immune system effects of natalizumab products may increase the risk for infections. In Study MS1 [see Clinical Studies (14.1)], certain types of infections, including pneumonias and urinary tract infections (including serious cases), gastroenteritis, vaginal infections, tooth infections, tonsillitis, and herpes infections, occurred more often in natalizumab-treated patients than in placebo-treated patients [see Warnings and Precautions (5.1) and Adverse Reactions (6.1)]. One opportunistic infection, a cryptosporidial gastroenteritis with a prolonged course, was observed in a patient who received natalizumab in Study MS1.

In Studies MS1 and MS2, an increase in infections was seen in patients concurrently receiving short courses of corticosteroids. However, the increase in infections in natalizumab-treated patients who received steroids was similar to the increase in placebo-treated patients who received steroids.

In a long-term safety study of patients treated with natalizumab for multiple sclerosis, opportunistic infections (pulmonary mycobacterium avium intracellulare, aspergilloma, cryptococcal fungemia and meningitis, and Candida pneumonia) have been observed in <1% of natalizumab-treated patients.

In CD clinical studies, opportunistic infections (pneumocystis carinii pneumonia, pulmonary mycobacterium avium intracellulare, bronchopulmonary aspergillosis, and burkholderia cepacia) have been observed in <1% of natalizumab-treated patients; some of these patients were receiving concurrent immunosuppressants [see Warnings and Precautions (5.1) and Adverse Reactions (6.1)].

In Studies CD1 and CD2, an increase in infections was seen in patients concurrently receiving corticosteroids. However, the increase in infections was similar in placebo-treated and natalizumab-treated patients who received steroids. Concurrent use of antineoplastic, immunosuppressant, or immunomodulating agents may further increase the risk of infections, including PML and other opportunistic infections, over the risk observed with use of natalizumab alone [see Warnings and Precautions (5.1) and Adverse Reactions (6.1)]. The safety and efficacy of natalizumab products in combination with antineoplastic, immunosuppressant, or immunomodulating agents have not been established. Patients receiving chronic immunosuppressant or immunomodulatory therapy or who have systemic medical conditions resulting in significantly compromised immune system function should not ordinarily be treated with natalizumab products. The risk of PML is also increased in patients who have been treated with an immunosuppressant prior to receiving natalizumab products [see Warnings and Precautions (5.1)].

For patients with Crohn's disease who start TYRUKO while on chronic corticosteroids, commence steroid withdrawal as soon as a therapeutic benefit has occurred. If the patient cannot discontinue systemic corticosteroids within six months, discontinue TYRUKO.

5.7 Laboratory Test Abnormalities

In clinical trials, natalizumab was observed to induce increases in circulating lymphocytes, monocytes, eosinophils, basophils, and nucleated red blood cells. Observed changes persisted during natalizumab exposure, but were reversible, returning to baseline levels usually within 16 weeks after the last dose. Elevations of neutrophils were not observed. Natalizumab induces mild decreases in hemoglobin levels (mean decrease of 0.6 g/dL) that are frequently transient.

5.8 Hematological Abnormalities

Cases of thrombocytopenia, including immune thrombocytopenic purpura (ITP), have been reported with the use of natalizumab products in the postmarketing setting. Symptoms of thrombocytopenia may include easy bruising, abnormal bleeding, and petechiae. Delay in the diagnosis and treatment of thrombocytopenia may lead to serious and life-threatening sequelae. If thrombocytopenia is suspected, TYRUKO should be discontinued.

Cases of neonatal thrombocytopenia and anemia have been reported in newborns with in utero exposure to natalizumab products [see Use in Specific Populations (8.1)]. A CBC should be obtained in neonates with in utero exposure to TYRUKO.

5.9 Immunizations

No data are available on the effects of vaccination in patients receiving natalizumab products. No data are available on the secondary transmission of infection by live vaccines in patients receiving natalizumab products.

6 ADVERSE REACTIONS

The following serious adverse reactions are described below and elsewhere in the labeling:

- Progressive Multifocal Leukoencephalopathy (PML) [see Warnings and Precautions (5.1)]
- Herpes Infections [see Warnings and Precautions (5.3)]
- Hepatotoxicity [see Warnings and Precautions (5.4)]
- Hypersensitivity/Antibody Formation [see Warnings and Precautions (5.5)]
- Immunosuppression/Infections [see Warnings and Precautions (5.6)]
- Hematological Abnormalities [see Warnings and Precautions (5.8)]

6.1 Clinical Trials Experience

Because clinical trials are conducted under widely varying conditions, adverse reaction rates observed in the clinical trials of a drug cannot be directly compared to rates in the clinical trials of another drug and may not reflect the rates observed in practice.

The most common adverse reactions (incidence ≥10%) were headache and fatigue in both the multiple sclerosis (MS) and Crohn’s disease (CD) studies. Other common adverse reactions (incidence ≥10%) in the MS population were arthralgia, urinary tract infection, lower respiratory tract infection, gastroenteritis, vaginitis, depression, pain in extremity, abdominal discomfort, diarrhea NOS, and rash. Other common adverse reactions (incidence ≥10%) in the CD population were upper respiratory tract infections and nausea.

The most frequently reported adverse reactions resulting in clinical intervention (i.e., discontinuation of natalizumab) in the MS studies were urticaria (1%) and other hypersensitivity reactions (1%), and in the CD studies (Studies CD1 and CD2) were the exacerbation of Crohn’s disease (4.2%) and acute hypersensitivity reactions (1.5%) [see Warnings and Precautions (5.5)].

A total of 1617 multiple sclerosis patients in controlled studies received natalizumab, with a median duration of exposure of 28 months. A total of 1563 patients received natalizumab in all CD studies for a median exposure of 5 months; of these patients, 33% (n=518) received at least one year of treatment and 19% (n=297) received at least two years of treatment.

Multiple Sclerosis Clinical Studies

The most common serious adverse reactions in Study MS1 [see Clinical Studies (14.1)] with natalizumab were infections (3.2% versus 2.6% in placebo, including urinary tract infection [0.8% versus 0.3%] and pneumonia [0.6% versus 0%]), acute hypersensitivity reactions (1.1% versus 0.3%, including anaphylaxis/anaphylactoid reaction [0.8% versus 0%]), depression (1.0% versus 1.0%, including suicidal ideation or attempt [0.6% versus 0.3%]), and cholelithiasis (1.0% versus 0.3%). In Study MS2, serious adverse reactions of appendicitis were also more common in patients who received natalizumab (0.8% versus 0.2% in placebo).

Table 2 enumerates adverse reactions and selected laboratory abnormalities that occurred in Study MS1 at an incidence of at least 1 percentage point higher in natalizumab-treated patients than was observed in placebo-treated patients.

Table 2: Adverse Reactions in Study MS1 (Monotherapy Study)
Adverse Reactions (Preferred Term) | Natalizumab (n=627) % | Placebo (n=312) %
General
Headache | 38 | 33
Fatigue | 27 | 21
Arthralgia | 19 | 14
Chest discomfort | 5 | 3
Other hypersensitivity reactions** | 5 | 2
Acute hypersensitivity reactions** | 4 | <1
Seasonal allergy | 3 | 2
Rigors | 3 | <1
Weight increased | 2 | <1
Weight decreased | 2 | <1
Infection
Urinary tract infection | 21 | 17
Lower respiratory tract infection | 17 | 16
Gastroenteritis | 11 | 9
Vaginitis* | 10 | 6
Tooth infections | 9 | 7
Herpes | 8 | 7
Tonsillitis | 7 | 5
Psychiatric
Depression | 19 | 16
Musculoskeletal/Connective Tissue Disorders
Pain in extremity Muscle cramp Joint swelling | 16 5 2 | 14 3 1
Gastrointestinal Abdominal discomfort Diarrhea NOS Abnormal liver function test | 11 10 5 | 10 9 4
Skin Rash Dermatitis Pruritus Night sweats | 12 7 4 1 | 9 4 2 0
Menstrual Disorders* Irregular menstruation Dysmenorrhea Amenorrhea Ovarian cyst | 5 3 2 2 | 4 <1 1 <1
Neurologic Disorders Vertigo Somnolence | 6 2 | 5 <1
Renal and Urinary Disorders Urinary urgency/frequency Urinary incontinence | 9 4 | 7 3
Injury Limb injury NOS Skin laceration Thermal burn | 3 2 1 | 2 <1 <1
*Percentage based on female patients only.
** Acute versus other hypersensitivity reactions are defined as occurring within 2 hours post-infusion versus more than 2 hours.

In Study MS2, peripheral edema was more common in patients who received natalizumab (5% versus 1% in placebo).

Crohn's Disease Clinical Studies

The following serious adverse reactions in the induction Studies CD1 and CD2 [see Clinical Studies (14.2)] were reported more commonly with natalizumab than placebo and occurred at an incidence of at least 0.3%: intestinal obstruction or stenosis (2% vs. 1% in placebo), acute hypersensitivity reactions (0.5% vs. 0%), abdominal adhesions (0.3% vs. 0%), and cholelithiasis (0.3% vs. 0%). Similar serious adverse reactions were seen in the maintenance Study CD3. Table 3 enumerates adverse reactions that occurred in Studies CD1 and CD2 (median exposure of 2.8 months). Table 4 enumerates adverse reactions that occurred in Study CD3 (median exposure of 11.0 months).

Table 3: Adverse Reactions in Studies CD1 and CD2 (Induction Studies)
Adverse Reactions* | Natalizumab n=983 % | Placebo n=431 %
General Headache Fatigue Arthralgia Influenza-like illness Acute hypersensitivity reactions Tremor | 32 10 8 5 2 1 | 23 8 6 4 <1 <1
Infection Upper respiratory tract infection Vaginal infections** Viral infection Urinary tract infection | 22 4 3 3 | 16 2 2 1
Respiratory Pharyngolaryngeal pain Cough | 6 3 | 4 <1
Gastrointestinal Nausea Dyspepsia Constipation Flatulence Aphthous stomatitis | 17 5 4 3 2 | 15 3 2 2 <1
Skin Rash Dry skin | 6 1 | 4 0
Menstrual Disorder Dysmenorrhea** | 2 | <1
* Occurred at an incidence of at least 1% higher in natalizumab-treated patients than placebo-treated patients.
** Percentage based on female patients only.

Table 4: Adverse Reactions in Study CD3 (Maintenance Study)
Adverse Reactions* | Natalizumab n=214 % | Placebo n=214 %
General Headache Influenza-like illness Peripheral edema Toothache | 37 11 6 4 | 31 6 3 <1
Infection Influenza Sinusitis Vaginal infections** Viral infection | 12 8 8 7 | 5 4 <1 3
Respiratory Cough | 7 | 5
Gastrointestinal Lower abdominal pain | 4 | 2
Musculoskeletal and Connective Tissue Back pain | 12 | 8
Menstrual Disorder Dysmenorrhea** | 6 | 3

* Occurred at an incidence of at least 2% higher in natalizumab -treated patients than placebo-treated patients.

** Percentage based on female patients only.

Infections

Progressive Multifocal Leukoencephalopathy (PML) occurred in three patients who received natalizumab in clinical trials [see Warnings and Precautions (5.1)]. Two cases of PML were observed in the 1,869 patients with multiple sclerosis who were treated for a median of 120 weeks. These two patients had received natalizumab in addition to interferon beta-1a [see Warnings and Precautions (5.1)]. The third case occurred after eight doses in one of the 1,043 patients with Crohn’s disease who were evaluated for PML. In the postmarketing setting, additional cases of PML have been reported in natalizumab-treated multiple sclerosis and Crohn’s disease patients who were not receiving concomitant immunomodulatory therapy.

In Studies MS1 and MS2 [see Clinical Studies (14.1)], the rate of any type of infection was approximately 1.5 per patient-year in both natalizumab-treated patients and placebo-treated patients. The infections were predominately upper respiratory tract infections, influenza, and urinary tract infections. In Study MS1, the incidence of serious infection was approximately 3% in natalizumab-treated patients and placebo-treated patients. Most patients did not interrupt treatment with natalizumab during infections. The only opportunistic infection in the multiple sclerosis clinical trials was a case of cryptosporidial gastroenteritis with a prolonged course.

In Studies CD1 and CD2 [see Clinical Studies (14.2)], the rate of any type of infection was 1.7 per patient-year in natalizumab-treated patients and 1.4 per patient-year in placebo-treated patients. In Study CD3, the incidence of any type of infection was 1.7 per patient-year in natalizumab-treated patients and was similar in placebo-treated patients. The most common infections were nasopharyngitis, upper respiratory tract infection, and influenza. The majority of patients did not interrupt natalizumab therapy during infections, and recovery occurred with appropriate treatment. Concurrent use of natalizumab in CD clinical trials with chronic steroids and/or methotrexate, 6-MP, and azathioprine did not result in an increase in overall infections compared to natalizumab alone; however, the concomitant use of such agents could lead to an increased risk of serious infections.

In Studies CD1 and CD2, the incidence of serious infection was approximately 2.1% in both natalizumab-treated patients and placebo-treated patients. In Study CD3, the incidence of serious infection was approximately 3.3% in natalizumab-treated patients and approximately 2.8% in placebo-treated patients.

In clinical studies for CD, opportunistic infections (pneumocystis carinii pneumonia, pulmonary mycobacterium avium intracellulare, bronchopulmonary aspergillosis, and burkholderia cepacia) have been observed in <1% of natalizumab-treated patients; some of these patients were receiving concurrent immunosuppressants [see Warnings and Precautions (5.6)]. Two serious non-bacterial meningitides occurred in natalizumab-treated patients compared to none in placebo-treated patients.

Infusion-related Reactions

An infusion-related reaction was defined in clinical trials as any adverse event occurring within two hours of the start of an infusion. In MS clinical trials, approximately 24% of natalizumab-treated multiple sclerosis patients experienced an infusion-related reaction, compared to 18% of placebo-treated patients. In the controlled CD clinical trials, infusion-related reactions occurred in approximately 11% of patients treated with natalizumab compared to 7% of placebo-treated patients. Reactions more common in the natalizumab-treated MS patients compared to the placebo-treated MS patients included headache, dizziness, fatigue, urticaria, pruritus, and rigors.

Acute urticaria was observed in approximately 2% of patients. Other hypersensitivity reactions were observed in 1% of patients receiving natalizumab. Serious systemic hypersensitivity infusion reactions occurred in <1% of patients [see Warnings and Precautions (5.5)]. All patients recovered with treatment and/or discontinuation of the infusion.

Infusion-related reactions that were more common in CD patients receiving natalizumab than those receiving placebo included headache, nausea, urticaria, pruritus, and flushing. Serious infusion reactions occurred in Studies CD1, CD2, and CD3 at an incidence of <1% in natalizumab-treated patients.

MS and CD patients who became persistently positive for antibodies to natalizumab were more likely to have an infusion-related reaction than those who were antibody-negative.

6.2 Immunogenicity

The observed incidence of anti-drug antibodies is highly dependent on the sensitivity and specificity of the assay. Differences in assay methods preclude meaningful comparisons of the incidence of anti-drug antibodies in the studies described below with the incidence of anti-drug antibodies in other studies, including those of natalizumab or of other natalizumab products.

Patients in Study MS1 [see Clinical Studies (14.1)] were tested for antibodies to natalizumab every 12 weeks. The assays used were unable to detect low to moderate levels of antibodies to natalizumab. Approximately 9% of patients receiving natalizumab developed detectable antibodies at least once during treatment. Approximately 6% of patients had positive antibodies on more than one occasion. Approximately 82% of patients who became persistently antibody-positive developed detectable antibodies by 12 weeks. Anti-natalizumab antibodies were neutralizing in vitro.

The presence of anti-natalizumab antibodies was correlated with a reduction in serum natalizumab levels. In Study MS1, the Week 12 pre-infusion mean natalizumab serum concentration in antibody-negative patients was 15 mcg/mL compared to 1.3 mcg/mL in antibody-positive patients. Persistent antibody-positivity resulted in a substantial decrease in the effectiveness of natalizumab. The risk of increased disability and the annualized relapse rate were similar in persistently antibody-positive natalizumab-treated patients and patients who received placebo. A similar phenomenon was also observed in Study MS2.

Infusion-related reactions that were most often associated with persistent antibody-positivity included urticaria, rigors, nausea, vomiting, headache, flushing, dizziness, pruritus, tremor, feeling cold, and pyrexia. Additional adverse reactions more common in persistently antibody-positive patients included myalgia, hypertension, dyspnea, anxiety, and tachycardia.

Patients in CD studies [see Clinical Studies (14.2)] were first tested for antibodies at Week 12, and in a substantial proportion of patients, this was the only test performed given the 12-week duration of placebo-controlled studies. Approximately 10% of patients were found to have anti‑natalizumab antibodies on at least one occasion. Five percent (5%) of patients had positive antibodies on more than one occasion. Persistent antibodies resulted in reduced efficacy and an increase in infusion-related reactions with symptoms that include urticaria, pruritus, nausea, flushing, and dyspnea.

The long-term immunogenicity of natalizumab products and the effects of low to moderate levels of antibody to natalizumab products are unknown [see Warnings and Precautions (5.5) and Adverse Reactions (6.1)].

6.3 Postmarketing Experience

The following adverse reactions have been identified during post approval use of natalizumab products. Because these reactions are reported voluntarily from a population of uncertain size, it is not always possible to reliably estimate their frequency or establish a causal relationship to drug exposure.

Blood disorders: hemolytic anemia, thrombocytopenia (including immune thrombocytopenic purpura) [see Warnings and Precautions (5.8)].

7 DRUG INTERACTIONS

Because of the potential for increased risk of PML and other infections, Crohn’s disease patients receiving natalizumab products should not be treated with concomitant immunosuppressants (e.g., 6‑ mercaptopurine, azathioprine, cyclosporine, or methotrexate) or inhibitors of TNF-α, and corticosteroids should be tapered in those patients with Crohn’s disease who are on chronic corticosteroids when they start TYRUKO therapy [see Indications and Usage (1.2) and Warnings and Precautions (5.1, 5.6)]. Ordinarily, MS patients receiving chronic immunosuppressant or immunomodulatory therapy should not be treated with TYRUKO [see Indications and Usage (1.1) and Warnings and Precautions (5.1, 5.6)].

8 USE IN SPECIFIC POPULATIONS

8.1 Pregnancy

Risk Summary

There are no adequate data on the risk of major birth defects, miscarriage, or other adverse maternal outcomes associated with the use of natalizumab products in pregnant women. Adverse fetal outcomes of neonatal thrombocytopenia and anemia have been reported (see Clinical Considerations). In animal studies, administration of natalizumab during pregnancy produced fetal immunologic and hematologic effects in monkeys at doses similar to the human dose and reduced offspring survival in guinea pigs at doses greater than the human dose. These doses were not maternally toxic but produced the expected pharmacological effects in maternal animals (see Data).

In the U.S. general population, the estimated background risk of major birth defects and miscarriage in clinically recognized pregnancies is 2-4% and 15-20%, respectively. The background risk of major birth defects and miscarriage for the indicated population is unknown.

Clinical Considerations

Fetal/Neonatal Adverse Reactions

Cases of neonatal thrombocytopenia and anemia in infants born to women exposed to natalizumab products during pregnancy were reported in the post-marketing setting [see Warnings and Precautions (5.8)]. Therefore, a CBC should be obtained in neonates who were exposed to TYRUKO in utero.

Data

Animal Data

In developmental toxicity studies conducted in guinea pigs and monkeys, at natalizumab doses up to 30 mg/kg (7 times the recommended human dose based on body weight [mg/kg]), transplacental transfer and in utero exposure of the embryo/fetus was demonstrated in both species.

In a study in which pregnant guinea pigs were administered natalizumab (0, 3, 10, or 30 mg/kg) by intravenous (IV) infusion on alternate days throughout organogenesis (gestation days [GD] 4‑30), no effects on embryofetal development were observed.

When pregnant monkeys were administered natalizumab (0, 3, 10, or 30 mg/kg) by IV infusion on alternative days throughout organogenesis (GDs 20-70), serum levels in fetuses at delivery were approximately 35% of maternal serum natalizumab levels. There were no effects on embryofetal development; however, natalizumab-related immunological and hematologic changes were observed in the fetuses at the two highest doses. These changes included decreases in lymphocytes (CD3+ and CD20+), changes in lymphocyte subpopulation percentages, mild anemia, reduced platelet count, increased spleen weights, and reduced liver and thymus weights associated with increased splenic extramedullary hematopoiesis, thymic atrophy, and decreased hepatic hematopoiesis.

In a study in which monkeys were exposed to natalizumab during pregnancy (IV infusion of 30 mg/kg) on alternate days from GD20 to GD70 or GD20 to term, abortions were increased approximately 2-fold compared to controls. In offspring born to mothers administered natalizumab on alternate days from GD20 until delivery, hematologic effects (decreased lymphocyte and platelet counts) were also observed. These effects were reversed upon clearance of natalizumab. There was no evidence of anemia in these offspring. Offspring exposed in utero and during lactation had a normal immune response to challenge with a T-cell dependent antigen.

In a study in which pregnant guinea pigs were exposed to natalizumab (30 mg/kg IV) on alternate dates during GDs 30-64, a reduction in pup survival was observed.

8.2 Lactation

Risk Summary

Natalizumab products have been detected in human milk. There are no data on the effects of this exposure on the breastfed infant or the effects of the drug on milk production.

The developmental and health benefits of breastfeeding should be considered along with the mother’s clinical need for TYRUKO and any potential adverse effects on the breastfed infant from TYRUKO or from the underlying maternal condition.

8.4 Pediatric Use

Safety and effectiveness in pediatric patients with multiple sclerosis or Crohn's disease below the age of 18 years have not been established. TYRUKO is not indicated for use in pediatric patients.

8.5 Geriatric Use

Clinical studies of natalizumab did not include sufficient numbers of patients aged 65 years and over to determine whether they respond differently than younger patients. Other reported clinical experience has not identified differences in responses between the elderly and younger patients.

10 OVERDOSAGE

Safety of doses higher than 300 mg has not been adequately evaluated. The maximum amount of natalizumab products that can be safely administered has not been determined.

11 DESCRIPTION

Natalizumab-sztn is a recombinant humanized IgG4ĸ monoclonal antibody produced in a Chinese hamster ovary (CHO) mammalian cell expression system. Natalizumab-sztn contains human framework regions and the complementarity-determining regions of an antibody that binds to α4-integrin. The molecular weight of natalizumab-sztn is 149 kilodaltons.

TYRUKO (natalizumab-sztn) injection is supplied as a sterile, preservative-free, colorless, and clear to slightly opalescent solution for intravenous infusion. Each 15 mL of solution contains 300 mg natalizumab-sztn; histidine (6.36 mg); L-histidine hydrochloride monohydrate (22.86 mg); polysorbate 80, USP/NF (3 mg); sodium chloride, USP (131.49 mg); and Water for Injection, USP at pH 5.7.

12 CLINICAL PHARMACOLOGY

12.1 Mechanism of Action

Natalizumab products bind to the α4-subunit of α4β1 and α4β7 integrins expressed on the surface of all leukocytes except neutrophils, and inhibits the α4-mediated adhesion of leukocytes to their counter-receptor(s). The receptors for the α4 family of integrins include vascular cell adhesion molecule-1 (VCAM-1), which is expressed on activated vascular endothelium, and mucosal addressin cell adhesion molecule-1 (MAdCAM-1) present on vascular endothelial cells of the gastrointestinal tract. Disruption of these molecular interactions prevents transmigration of leukocytes across the endothelium into inflamed parenchymal tissue. In vitro, anti-α4-integrin antibodies also block α4‑mediated cell binding to ligands such as osteopontin and an alternatively spliced domain of fibronectin, connecting segment-1 (CS-1). In vivo, natalizumab products may further act to inhibit the interaction of α4-expressing leukocytes with their ligand(s) in the extracellular matrix and on parenchymal cells, thereby inhibiting further recruitment and inflammatory activity of activated immune cells.

The specific mechanism(s) by which natalizumab products exert their effects in multiple sclerosis and Crohn’s disease have not been fully defined.

In multiple sclerosis, lesions are believed to occur when activated inflammatory cells, including T-lymphocytes, cross the blood-brain barrier (BBB). Leukocyte migration across the BBB involves interaction between adhesion molecules on inflammatory cells and their counter-receptors present on endothelial cells of the vessel wall. The clinical effect of natalizumab products in multiple sclerosis may be secondary to blockade of the molecular interaction of α4β1-integrin expressed by inflammatory cells with VCAM-1 on vascular endothelial cells, and with CS-1 and/or osteopontin expressed by parenchymal cells in the brain. Data from an experimental autoimmune encephalitis animal model of multiple sclerosis demonstrate reduction of leukocyte migration into brain parenchyma and reduction of plaque formation detected by magnetic resonance imaging (MRI) following repeated administration of natalizumab. The clinical significance of these animal data is unknown.

In Crohn’s disease, the interaction of the α4β7-integrin with the endothelial receptor MAdCAM‑1 has been implicated as an important contributor to the chronic inflammation that is a hallmark of the disease. MAdCAM-1 is mainly expressed on gut endothelial cells and plays a critical role in the homing of T lymphocytes to gut lymph tissue found in Peyer’s patches. MAdCAM-1 expression has been found to be increased at active sites of inflammation in patients with CD, which suggests it may play a role in the recruitment of leukocytes to the mucosa and contribute to the inflammatory response characteristic of CD. The clinical effect of natalizumab products in CD may therefore be secondary to blockade of the molecular interaction of the α4β7-integrin receptor with MAdCAM-1 expressed on the venular endothelium at inflammatory foci. VCAM-1 expression has been found to be upregulated on colonic endothelial cells in a mouse model of IBD and appears to play a role in leukocyte recruitment to sites of inflammation. The role of VCAM-1 in CD, however, is not clear.

12.2 Pharmacodynamics

Administration of natalizumab products increases the number of circulating leukocytes (including lymphocytes, monocytes, basophils, and eosinophils) due to inhibition of transmigration out of the vascular space. Natalizumab products do not affect the absolute count of circulating neutrophils [see Warnings and Precautions (5.7)].

12.3 Pharmacokinetics

Multiple Sclerosis (MS) Patients

In patients with MS, following the repeat intravenous administration of a 300 mg dose of natalizumab, the mean ± SD maximum observed serum concentration was 110 ± 52 mcg/mL. Mean average steady-state trough concentrations ranged from 23 mcg/mL to 29 mcg/mL. The observed time to steady-state was approximately 24 weeks after every four weeks of dosing. The mean ± SD half-life, volume of distribution, and clearance of natalizumab were 11 ± 4 days, 5.7 ± 1.9 L, and 16 ± 5 mL/hour, respectively.

The effects of covariates such as body weight, age, gender, and presence of anti-natalizumab antibodies on natalizumab pharmacokinetics were investigated in a population pharmacokinetic study (n=2,195). Natalizumab clearance increased with body weight in a less than proportional manner such that a 43% increase in body weight resulted in a 32% increase in clearance. The presence of persistent anti-natalizumab antibodies increased natalizumab clearance approximately 3-fold [see Adverse Reactions (6.2)].

Crohn's Disease (CD) Patients

In patients with CD, following the repeat intravenous administration of a 300 mg dose of natalizumab, the mean ± SD maximum observed serum concentration was 101 ± 34 mcg/mL. The mean ± SD average steady-state trough concentration was 10 ± 9 mcg/mL. The estimated time to steady-state was approximately 16 to 24 weeks after every four weeks of dosing. The mean ± SD half-life, volume of distribution, and clearance of natalizumab were 10 ± 7 days, 5.2 ± 2.8 L, and 22 ± 22 mL/hour, respectively.

The effects of total body weight, age, gender, race, selected hematology and serum chemistry measures, co-administered medications (infliximab, immunosuppressants, or steroids), and the presence of anti-natalizumab antibodies were investigated in a population pharmacokinetic analysis (n=1156). The presence of anti-natalizumab antibodies was observed to increase natalizumab clearance [see Adverse Reactions (6.2)].

Pharmacokinetics of natalizumab products in patients with renal or hepatic insufficiency have not been studied.

13 NONCLINICAL TOXICOLOGY

13.1 Carcinogenesis, Mutagenesis, Impairment of Fertility

No clastogenic or mutagenic effects of natalizumab were observed in the Ames test or in vitro chromosomal aberration assay in human lymphocytes. Natalizumab showed no effects in in vitro assays of α4-integrin positive human tumor line proliferation/cytotoxicity. Xenograft transplantation models in SCID and nude mice with two α4-integrin positive human tumor lines (leukemia, melanoma) demonstrated no increase in tumor growth rates or metastasis resulting from natalizumab treatment.

In male guinea pigs administered natalizumab (0, 3, 10, or 30 mg/kg) by intravenous (IV) infusion on alternate days from 28 days prior to and continuing throughout mating (to untreated females), no effects on fertility were observed. The highest dose tested is 6 times the recommended human dose (RHD) (300 mg) on a body weight (mg/kg) basis.

In a separate study in female guinea pigs (mated with untreated males), natalizumab (0, 3, 10, or 30 mg/kg), administered by IV infusion on alternate days from gestation day (GD) 30 of the first pregnancy through GD 30 of the second pregnancy, resulted in a decrease in pregnancy rate and number of implantations at 30 mg/kg. (Fertility parameters were assessed for the second pregnancy.) The no-effect dose for effects on female fertility (10 mg/kg) is 2 times the RHD on a body weight basis.

14 CLINICAL STUDIES

14.1 Multiple Sclerosis

Natalizumab was evaluated in two randomized, double-blind, placebo-controlled trials in patients with multiple sclerosis. Both studies enrolled patients who experienced at least one clinical relapse during the prior year and had a Kurtzke Expanded Disability Status Scale (EDSS) score between 0 and 5.0. Results for each study are shown in Table 5 and Table 6. Median time on study drug was 120 weeks in each study. In both studies, neurological evaluations were performed every 12 weeks and at times of suspected relapse. Magnetic resonance imaging evaluations for T1-weighted gadolinium (Gd)-enhancing lesions and T2-hyperintense lesions were performed annually.

Study MS1 enrolled patients who had not received any interferon-beta or glatiramer acetate for at least the previous 6 months; approximately 94% had never been treated with these agents.

Median age was 37, with a median disease duration of 5 years. Patients were randomized in a 2:1 ratio to receive natalizumab 300 mg intravenous infusion (n=627) or placebo (n=315) every 4 weeks for up to 28 months (30 infusions).

Study MS2 enrolled patients who had experienced one or more relapses while on treatment with AVONEX® (Interferon beta-1a) 30 mcg intramuscularly (IM) once weekly during the year prior to study entry. Median age was 39, with a median disease duration of 7 years. Patients were evenly randomized to receive natalizumab 300 mg (n=589) or placebo (n=582) every 4 weeks for up to 28 months (30 infusions). All patients continued to receive AVONEX ® 30 mcg IM once weekly. The efficacy of natalizumab alone was not compared with the efficacy of natalizumab plus AVONEX ®.

The primary endpoint at 2 years was time to onset of sustained increase in disability, defined as an increase of at least 1 point on the EDSS from baseline EDSS ≥1.0 that was sustained for 12 weeks, or at least a 1.5 point increase on the EDSS from baseline EDSS=0 that was sustained for 12 weeks. Time to onset of sustained increase in disability was longer in natalizumab-treated patients than in placebo-treated patients in Studies MS1 (Figure 1) and MS2. The proportion of patients with increased disability and the annualized relapse rate were also lower in natalizumab-treated patients than in placebo-treated patients in Studies MS1 and MS2 (Table 5 and Table 6).

Table 5: Clinical and MRI Endpoints in Study MS1 (Monotherapy Study) at 2 Years
 | Natalizumab (n=627) | Placebo (n=315)
CLINICAL ENDPOINTS
Percentage with sustained increase in disability | 17% | 29%
Relative Risk Reduction | 42% (95% CI 23%, 57%)
Annualized relapse rate | 0.22 | 0.67
Relative reduction (percentage) | 67%
Percentage of patients remaining relapse-free | 67% | 41%
MRI ENDPOINTS
New or newly enlarging T2-hyperintense lesions
Median | 0.0 | 5.0
Percentage of patients with*:
0 lesions | 57% | 15%
1 lesion | 17% | 10%
2 lesions | 8% | 8%
3 or more lesions | 18% | 68%
Gd-enhancing lesions
Median | 0.0 | 0.0
Percentage of patients with:
0 lesions | 97% | 72%
1 lesion | 2% | 12%
2 or more lesions | 1% | 16%
All analyses were intent-to-treat. For each endpoint, p<0.001. Determination of p-values: Increase in disability by Cox proportional hazards model adjusted for baseline EDSS and age; relapse rate by Poisson regression adjusting for baseline relapse rate, EDSS, presence of Gd-enhancing lesions, age; percentage relapse-free by logistic regression adjusting for baseline relapse rate; and lesion number by ordinal logistic regression adjusting for baseline lesion number.
Annualized relapse rate is calculated as the number of relapses for each subject divided by the number of years followed in the study for that subject. The value reported is the mean across all subjects.
*Values do not total 100% due to rounding.

Table 6: Clinical and MRI Endpoints in Study MS2 (Add-On Study) at 2 Years
 | Natalizumab plus AVONEX (n= 589) | Placebo plus AVONEX (n=582)
CLINICAL ENDPOINTS
Percentage with sustained increase in disability | 23% | 29%
Relative Risk Reduction | 24% (95% CI 4%, 39%)
Annualized relapse rate | 0.33 | 0.75
Relative reduction (percentage) | 56%
Percentage of patients remaining relapse-free | 54% | 32%
MRI ENDPOINTS
New or newly enlarging T2-hyperintense lesions
Median | 0.0 | 3.0
Percentage of patients with*:
0 lesions | 67% | 30%
1 lesion | 13% | 9%
2 lesions | 7% | 10%
3 or more lesions | 14% | 50%
Gd-enhancing lesions
Median | 0.0 | 0.0
Percentage of patients with*:
0 lesions | 96% | 75%
1 lesion | 2% | 12%
2 or more lesions | 1% | 14%
All analyses were intent-to-treat. For disability accumulation p=0.024, for all other endpoints, p<0.001. Determination of p-values: Increase in disability by Cox proportional hazards model adjusted for baseline EDSS; relapse rate by Poisson regression adjusting for baseline relapse rate, EDSS, presence of Gd-enhancing lesions, age; percentage relapse-free by logistic regression adjusting for baseline relapse rate; and lesion number by ordinal logistic regression adjusting for baseline lesion number.
Annualized relapse rate is calculated as the number of relapses for each subject divided by the number of years followed in the study for that subject. The value reported is the mean across all subjects.
*Values do not total 100% due to rounding.

14.2 Crohn's Disease

The safety and efficacy of natalizumab were evaluated in three randomized, double-blind, placebo-controlled clinical trials in 1414 adult patients with moderately to severely active Crohn’s disease (Crohn’s Disease Activity Index [CDAI] ≥220 and ≤450) [see References (15)].

Concomitant inhibitors of TNF-α were not permitted. Concomitant stable doses of aminosalicylates, corticosteroids, and/or immunosuppressants (e.g., 6-mercatopurine, azathioprine, or methotrexate) were permitted, and 89% of patients continued to receive at least one of these medications. Although permitted in the clinical trials, combination therapy with immunosuppressants is not recommended [see Indications and Usage (1.2)]. Overall, approximately two-thirds of patients were not taking concomitant immunosuppressants, and approximately one-third of patients were taking neither concomitant immunosuppressants nor concomitant corticosteroids.

Induction of clinical response (defined as ≥70-point decrease in CDAI from baseline) was evaluated in two studies. In Study CD1, 896 patients were randomized 4:1 to receive three monthly infusions of either 300 mg natalizumab or placebo. Clinical results were assessed at Week 10, and patients with incomplete information were considered as not having a clinical response. At Week 10, 56% of the 717 patients receiving natalizumab were in response compared to 49% of the 179 patients receiving placebo (treatment effect: 7%; 95% confidence interval (CI): [-1%, 16%]; p=0.067). In a post hoc analysis of the subset of 653 patients with elevated baseline C-reactive protein (CRP), indicative of active inflammation, 57% of natalizumab patients were in response compared to 45% of those receiving placebo (treatment effect: 12%; 95% CI: [3%, 22%]; nominal p=0.01).

In the second induction trial, Study CD2, only patients with elevated serum C-reactive Protein (CRP) were studied. A total of 509 patients were randomized 1:1 to receive three monthly infusions of either 300 mg natalizumab or placebo. In Study CD2, in contrast to Study CD1, clinical response and clinical remission (defined as CDAI score <150) were required to be met at both Weeks 8 and 12, rather than at a single time-point; patients with incomplete information were considered as not having a response (Table 7).

Table 7: Induction of Clinical Response and Remission in Study CD2
 | Natalizumab (n=259) | Placebo (n=250) | Treatment Difference (95% CI)
Clinical Response at: Week 8 Week 12 Both Weeks 8 & 12* | 56% 60% 48% | 40% 44% 32% | 16% (8%, 26%) 16% (7%, 25%) 16% (7%, 24%)
Clinical Remission at: Week 8 Week 12 Both Weeks 8 & 12* | 32% 37% 26% | 21% 25% 16% | 11% (3%, 19%) 12% (4%, 21%) 10% (3%, 18%)
*p <0.005
Response is defined as a ≥70-point reduction in CDAI score from baseline.
Remission is defined as CDAI <150.

In studies CD1 and CD2, for subgroups defined by prior use of, or by inadequate response to prior therapies (i.e., corticosteroids, immunosuppressants, and inhibitors of TNF-α), the treatment effect was generally similar to that seen in the whole study population. In the subgroup of patients that were taking neither concomitant immunosuppressants nor concomitant corticosteroids, the treatment effect was generally similar to that seen in the whole study population. Patients with inadequate response to inhibitors of TNF-α appeared to have lower clinical response and lower clinical remission in both the treatment and placebo groups. For patients in Study CD2 with an inadequate response to prior treatment with inhibitors of TNF-α, clinical response at both Weeks 8 and 12 was seen in 38% of those randomized to natalizumab, and clinical remission at both Weeks 8 and 12 was seen in 17%.

Maintenance therapy was evaluated in Study CD3. In this study, 331 patients from Study CD1 that had had a clinical response to natalizumab at both Weeks 10 and 12 were re-randomized 1:1 to treatment with continuing monthly infusions of either 300 mg natalizumab or placebo.

Maintenance of response was assessed by the proportion of patients who did not lose clinical response at any study visit for an additional 6 and 12 months of treatment (i.e., Month 9 and Month 15 after initial treatment with natalizumab). The study also assessed the proportion of patients who did not lose clinical remission at any study visit within the subset of those who were in remission at study entry. Requiring maintenance of response or remission at each visit, as opposed to just at Month 9 or Month 15, may result in lower proportions meeting endpoint criteria, and may make a comparison of these results with those of other products used to treat Crohn’s disease misleading (Table 8).

Table 8: Maintenance of Clinical Response and Remission in Study CD3
 | Natalizumab | Placebo | Treatment Difference (95% CI)
Clinical Response through: Month 9* Month 15 | (n=164) 61% 54% | (n=167) 29% 20% | 32% (21%, 43%) 34% (23%, 44%)
Clinical Remission through: Month 9* Month 15 | (n=128†) 45% 40% | (n=118†) 26% 15% | 19% (6%, 31%) 25% (13%, 36%)
*p<0.005
†Number of patients included for analysis of “through” Month 9 and Month 15 includes only those in remission upon entry into Study CD3.
Response is defined as CDAI <220 and a ≥70-point reduction in CDAI score compared to Baseline from Study CD1.
Remission is defined as CDAI <150.

For subgroups in study CD3 defined by prior use of, or by inadequate response to prior therapies (i.e., corticosteroids, immunosuppressants, and inhibitors of TNF-α), the treatment effect was generally similar to that seen in the whole study population. In the subgroup of patients that were taking neither concomitant immunosuppressants nor concomitant corticosteroids, the treatment effect was generally similar to that seen in the whole study population. Patients with inadequate response to inhibitors of TNF-α appeared to have lower maintenance of clinical response and lower maintenance of clinical remission in both the treatment and placebo groups. For patients in study CD3 with an inadequate response to prior treatment with inhibitors of TNF-α, maintenance of clinical response through Month 9 was seen in 52% of those randomized to natalizumab, and maintenance of clinical remission through Month 9 was seen in 30%.

Given the requirement to discontinue chronic steroids it is important to note that in the subgroup of patients (n=65) who were receiving corticosteroid medication at baseline, responded to natalizumab in Study CD1, and were re-randomized to natalizumab in Study CD3, approximately two-thirds were able to discontinue steroids within 10 weeks of initiating a steroid taper.

15 REFERENCES

- Best WR, Becktel JM, Singleton JW, Kern F: Development of a Crohn's Disease Activity Index, National Cooperative Crohn's Disease Study. Gastroenterology 1976; 70(3): 439-444.

16 HOW SUPPLIED/STORAGE AND HANDLING

TYRUKO (natalizumab-sztn) injection, a sterile, preservative-free, colorless and clear to slightly opalescent solution for dilution prior to intravenous infusion, is supplied as one 300 mg/15 mL (20 mg/mL) single-dose vial per carton (NDC 61314-543-94).

TYRUKO is available only through registered infusion centers participating in the TYRUKO REMS Program. To locate these infusion centers, contact Sandoz Inc. at 1-800-525-8747.

TYRUKO single-dose vials must be refrigerated between 2°C to 8°C (36°F to 46°F). Do not use beyond the expiration date stamped on the carton and vial label. DO NOT SHAKE OR FREEZE. Protect from light.

Store diluted TYRUKO solution refrigerated at 2°C to 8°C (36°F to 46°F) [see Dosage and Administration(2.3)].

17 PATIENT COUNSELING INFORMATION

Advise the patient to read the FDA-approved patient labeling (Medication Guide).

General Counseling Information

Counsel patients to understand the risks and benefits of TYRUKO before an initial prescription is written. The patient may be educated by either the enrolled prescriber or a healthcare provider under that prescriber's direction. INSTRUCT PATIENTS USING TYRUKO TO:

- Read the Medication Guide before starting TYRUKO and before each TYRUKO infusion
- Promptly report any new or continuously worsening symptoms that persist over several days to their prescriber [see Warnings and Precautions (5.1)]
- Inform all of their physicians that they are receiving TYRUKO
- Plan to see their prescriber three months after the first infusion, six months after the first infusion, every six months thereafter, and for at least six months after discontinuing TYRUKO

Progressive Multifocal Leukoencephalopathy

Inform patients that Progressive Multifocal Leukoencephalopathy (PML) has occurred in patients who received natalizumab products. Instruct the patient of the importance of contacting their doctor if they develop any symptoms suggestive of PML. Instruct the patient that typical symptoms associated with PML are diverse, progress over days to weeks, and include progressive weakness on one side of the body or clumsiness of limbs, disturbance of vision, and changes in thinking, memory, and orientation leading to confusion and personality changes. Instruct the patient that the progression of deficits usually leads to death or severe disability over weeks or months.

Instruct patients to continue to look for new signs and symptoms suggestive of PML for approximately 6 months following discontinuation of TYRUKO [see Warnings and Precautions (5.1)].

TYRUKO REMS Program

Advise the patient that TYRUKO is only available through a restricted program called the TYRUKO REMS Program. Inform the patient of the following requirements:

Patients must read the Medication Guide and sign the Patient Enrollment Form. Advise patients that TYRUKO is available only from certified pharmacies and infusion centers participating in the program [see Warnings and Precautions (5.2)].

Herpes Infections

Inform patients that TYRUKO increases the risk of developing encephalitis, and meningitis, which could be fatal, and acute retinal necrosis, which could lead to blindness, caused by the family of herpes viruses (e.g., herpes simplex and varicella zoster viruses). Instruct patients to immediately report any possible symptoms of encephalitis and meningitis (such as fever, headache, and confusion) or acute retinal necrosis (such as decreased visual acuity, eye redness, or eye pain) [see Warnings and Precautions (5.3)].

Hepatotoxicity

Inform patients that TYRUKO may cause liver injury. Instruct patients treated with TYRUKO to report promptly any symptoms that may indicate liver injury, including fatigue, anorexia, right upper abdominal discomfort, dark urine, or jaundice [see Warnings and Precautions (5.4)].

Hypersensitivity Reactions

Instruct patients to report immediately if they experience symptoms consistent with a hypersensitivity reaction (e.g., urticaria with or without associated symptoms) during or following an infusion of TYRUKO [see Warnings and Precautions (5.5)].

Immunosuppression/Infections

Inform patients that TYRUKO may lower the ability of their immune system to fight infections. Instruct the patient of the importance of contacting their doctor if they develop any symptoms of infection [see Warnings and Precautions (5.6)].

Hematological Abnormalities

Inform patients that TYRUKO may cause a low platelet count, which can cause severe bleeding that may be life-threatening. Instruct patients to report any symptoms that may indicate thrombocytopenia, such as easy bruising, prolonged bleeding from cuts, petechiae, abnormally heavy menstrual periods, or bleeding from the nose or gums that is new. Advise patients that TYRUKO may cause low platelet or red blood cell counts in neonates exposed to TYRUKO during pregnancy [see Warnings and Precautions (5.8)].

Pregnancy

Instruct patients that if they become pregnant or plan to become pregnant while taking TYRUKO they should inform their healthcare provider [see Use in Specific Populations (8.1)].

TYRUKO (natalizumab-sztn)

Manufactured by: Sandoz Inc.
Princeton, NJ 08540

US License No. 2003

All third party trademarks are the property of their respective owners.

Medication Guide

TYRUKO®(tie-ROO-koh)
(natalizumab-sztn)
injection, for intravenous use

Read this Medication Guide before you start receiving TYRUKO and before you receive each dose. There may be new information. This Medication Guide does not take the place of talking to your doctor about your medical condition or your treatment.

What is the most important information I should know about TYRUKO?

- TYRUKO increases your chance (risk) of getting a rare brain infection that usually leads to death or severe disability. This infection is called progressive multifocal leukoencephalopathy (PML). If PML happens, it usually happens in people with weakened immune systems.
- There is no known treatment, prevention, or cure for PML.
- Your chance of getting PML may be higher if you are also being treated with other medicines that can weaken your immune system, including other treatments for Multiple Sclerosis (MS) and Crohn’s disease (CD). You should not take certain medicines that weaken your immune system at the same time you are taking TYRUKO. Even if you use TYRUKO alone to treat your MS or CD, you can still get PML.
- Your risk of getting PML is higher if you:
- have been infected by the John Cunningham Virus (JCV). JCV is a common virus that is harmless in most people but can cause PML in people who have weakened immune systems, such as people taking TYRUKO. Most people who are infected by JCV do not know it or do not have any symptoms. This infection usually happens in childhood. Before you start receiving TYRUKO or during your treatment, your doctor may do a blood test to check if you have been infected by JCV.
- have received TYRUKO for a long time, especially longer than 2 years.
- have received certain medicines that can weaken your immune system before you start receiving TYRUKO.
Your risk of getting PML is greatest if you have all 3 risk factors listed above. There may be other risk factors for getting PML during TYRUKO treatment that we do not know about yet. Your doctor should discuss the risks and benefits of TYRUKO treatment with you before you decide to receive TYRUKO. See “What are the possible side effects of TYRUKO?”
- While you receive TYRUKO, and for 6 months after you stop receiving TYRUKO, it is important that you call your doctor right away if you have any new or worsening medical problems that have lasted several days.
  These may be new or sudden and include problems with:
  - thinking
  - eyesight
  - strength
  - balance
  - weakness on 1 side of your body
  - using your arms and legs

Tell all your doctors that you are receiving TYRUKO.

- Because of your risk of getting PML while you receive TYRUKO, TYRUKO is available only through a restricted distribution program called the TYRUKO REMS Program. To receive TYRUKO, you must talk to your doctor and understand the risks and benefits of TYRUKO and agree to follow all of the instructions in the TYRUKO REMS Program.
- TYRUKO is only:
- prescribed by doctors who are enrolled in the TYRUKO REMS Program.
- given by an infusion nurse from an infusion center that is enrolled in the TYRUKO REMS Program.
- given to people who are enrolled in the TYRUKO REMS Program.
- Before you receive TYRUKO, your doctor will:
- explain the TYRUKO REMS Program to you.
- have you sign the TYRUKO REMS Patient Enrollment Form.

What is TYRUKO?

TYRUKO is a prescription medicine used to treat adults with:

- relapsing forms of Multiple Sclerosis (MS), to include clinically isolated syndrome, relapsing-remitting disease and active secondary progressive disease. TYRUKO increases the risk of PML. When starting and continuing treatment with TYRUKO, it is important that you discuss with your doctor whether the expected benefit of TYRUKO is enough to outweigh this risk. See “What is the most important information I should know about TYRUKO?”
- moderate to severe Crohn’s disease (CD). TYRUKO is used:
- to reduce signs and symptoms of CD.
- in people who have not been helped enough by, or cannot use the usual CD medicines and medicines called tumor necrosis factor (TNF) inhibitors.

It is not known if TYRUKO is safe and effective in children under 18 years of age.

Who should not receive TYRUKO?

Do not receive TYRUKO if you:

- have PML.
- are allergic to natalizumab products or any of the ingredients in TYRUKO. See the end of this Medication Guide for a complete list of ingredients in TYRUKO.

Talk to your doctor before receiving TYRUKO if you have any of these conditions.

What should I tell my doctor before receiving each dose of TYRUKO?

Before you receive TYRUKO, tell your doctor if you:

- have medical conditions that can weaken your immune system, including:
  - HIV infection or AIDS
  - leukemia or lymphoma
  - an organ transplant
  - other medical conditions that can weaken your immune system
- have any new or worsening medical problems that have lasted several days. These may be new or sudden and include problems with:
  - thinking
  - eyesight
  - strength
  - balance
  - weakness on 1 side of your body
  - using your arms and legs
- have had hives, itching or trouble breathing during or after receiving a dose of TYRUKO.
- have a fever or infection (including shingles or any unusually long lasting infection).
- are pregnant or plan to become pregnant. TYRUKO may cause low platelets (thrombocytopenia) and low red blood cells (anemia), in your newborn baby if you take TYRUKO while you are pregnant. It is not known if TYRUKO can cause birth defects.
- are breastfeeding or plan to breastfeed. TYRUKO can pass into your breast milk. It is not known if the TYRUKO that passes into your breast milk can harm your baby. Talk to your doctor about the best way to feed your baby while you receive TYRUKO.

Tell your doctor about all the medicines you take, including prescription medicines, over-the-counter medicines, vitamins, and herbal supplements. Especially tell your doctor if you take medicines that can weaken your immune system. Ask your doctor if you are not sure.
Know the medicines you take. Keep a list of them to show your doctor and pharmacist when you get a new medicine.

How should I receive TYRUKO?

- TYRUKO is given 1 time every 4 weeks through a needle placed in your vein (IV infusion). Each infusion will last about 1 hour.
- Before each TYRUKO dose you will be asked questions to make sure TYRUKO is still right for you.

What are the possible side effects of TYRUKO?

TYRUKO may cause serious side effects, including:

- See "What is the most important information I should know about TYRUKO?"
- Herpes Infections. TYRUKO may increase your risk of getting an infection of the brain or the covering of your brain and spinal cord (encephalitis or meningitis) caused by herpes viruses that may lead to death. Call your doctor right away if you have sudden fever, severe headache, or if you feel confused after receiving TYRUKO. Herpes infections of the eye, causing blindness in some patients, have also occurred. Call your doctor right away if you have changes in vision, eye redness, or eye pain.
- Liver damage. Symptoms of liver damage can include:
  - yellowing of the skin and eyes (jaundice)
  - nausea
  - vomiting
  - unusual darkening of the urine
  - feeling tired or weak
Call your doctor right away if you have symptoms of liver damage. Your doctor can do blood tests to check for liver damage.
- Allergic reactions, including serious allergic reactions. Symptoms of an allergic reaction can include:
  - hives
  - itching
  - trouble breathing
  - chest pain
  - dizziness
  - wheezing
  - chills
  - rash
  - nausea
  - flushing of skin
  - low blood pressure
Serious allergic reactions usually happen within 2 hours of the start of your infusion, but they can happen at any time after you receive TYRUKO.
  Tell your doctor right away if you have any symptom of an allergic reaction, even if it happens after your infusion. You may need treatment if you are having an allergic reaction.
- Infections. TYRUKO may increase your chance of getting an unusual or serious infection because TYRUKO can weaken your immune system. You have a higher risk of getting infections if you also take other medicines that can weaken your immune system.
- Low platelet counts. TYRUKO may cause the number of platelets in your blood to be reduced. Call your healthcare provider if you have any of the following symptoms:
- easy bruising
- heavier menstrual periods than are normal
- bleeding from your gums or nose that is new or takes longer than usual to stop
- bleeding from a cut that is hard to stop
- small scattered red spots on your skin that are red, pink, or purple

The most common side effects of TYRUKO include:

- headache
- feeling tired
- urinary tract infection
- joint pain
- lung infection
- depression
- pain in your arms and legs
- diarrhea
- vaginitis
- rash
- nose and throat infections
- nausea
- stomach area pain

Tell your doctor about any side effect that bothers you or that does not go away.
These are not all the possible side effects of TYRUKO. Ask your doctor for more information.
Call your doctor for medical advice about side effects. You may report side effects to FDA at 1-800-FDA-1088.

General information about the safe and effective use of TYRUKO.

Medicines are sometimes prescribed for purposes other than those listed in a Medication Guide.

This Medication Guide summarizes the most important information about TYRUKO. If you would like more information, talk with your doctor. You can ask your pharmacist or doctor for information about TYRUKO that is written for healthcare professionals.

What are the ingredients in TYRUKO?

Active ingredient: natalizumab-sztn.

Inactive ingredients: histidine, L-histidine hydrochloride monohydrate; polysorbate 80, sodium chloride and water for injection.

Manufactured by: Sandoz Inc., Princeton, NJ 08540, US License No. 2003

For more information, go to www.tyruko.com or call 1-800-525-8747.

This Medication Guide has been approved by the U.S. Food and Drug Administration. Revised: 10/2025

PRINCIPAL DISPLAY PANEL - Carton Label

NDC 61314-543-94

Rx Only

TYRUKO®

(natalizumab-sztn)

injection

300 mg/ 15 mL (20 mg/mL)

For Intravenous Infusion Only.

Must be diluted prior to use.

One single-dose vial.

Discard unused portion.

ATTENTION PHARMACIST:

Each patient is required to receive

the enclosed Medication Guide.

SANDOZ